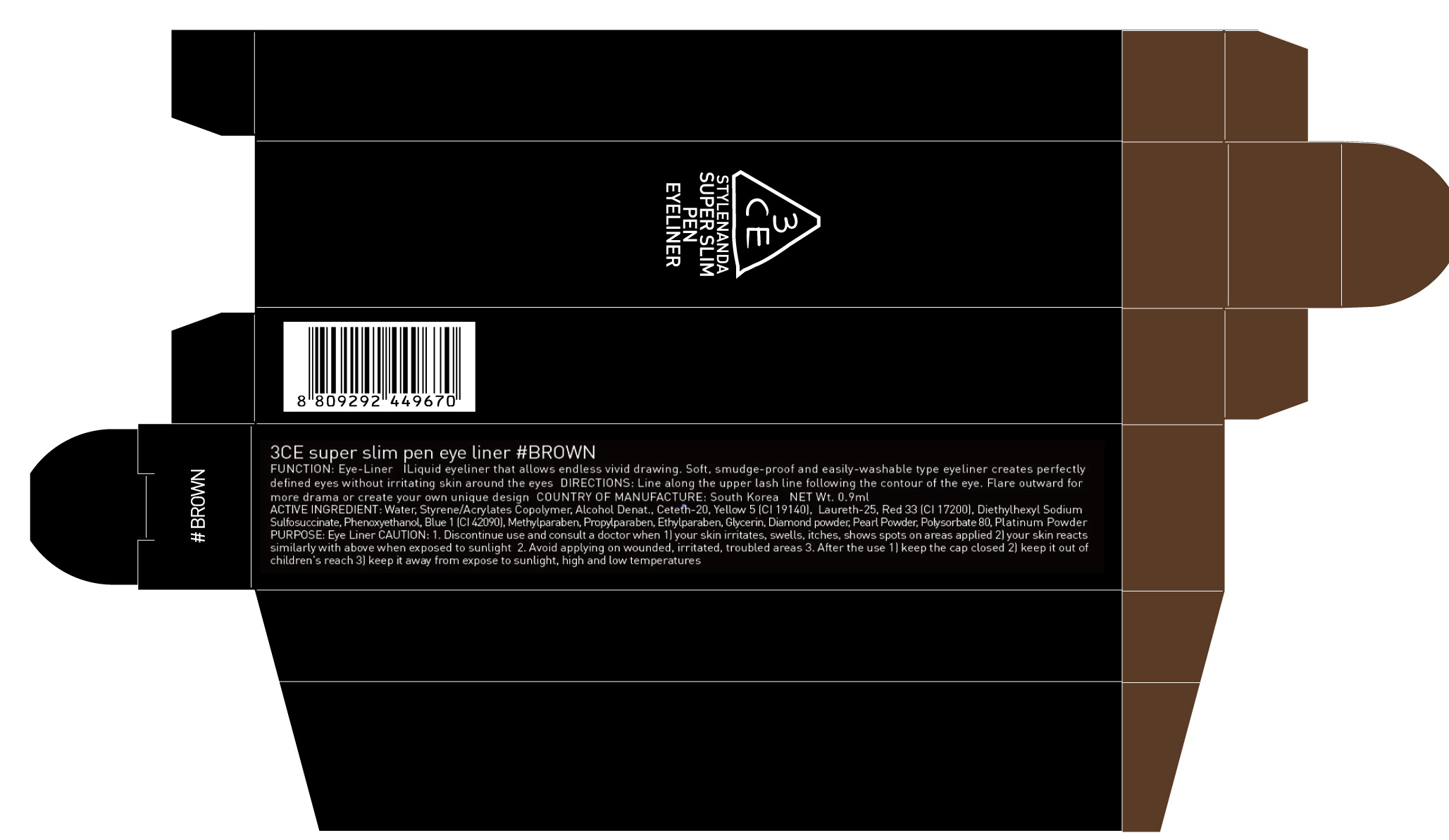 DRUG LABEL: 3CE SUPER SLIM PEN EYE LINER BROWN
NDC: 60764-018 | Form: LIQUID
Manufacturer: Nanda Co., Ltd
Category: otc | Type: HUMAN OTC DRUG LABEL
Date: 20160921

ACTIVE INGREDIENTS: Butylene Glycol 0.05 g/0.9 mL
INACTIVE INGREDIENTS: Water; Ceteth-20

ACTIVE INGREDIENT

Active Ingredient: Butylene Glycol 6.0%

INACTIVE INGREDIENT

Inactive Ingredients: Water, Styrene/Acrylates Copolymer, Alcohol Denat., Ceteth-20, Yellow 5 (CI 19140), Laureth-25, Red 33 (CI 17200), Diethylhexyl Sodium Sulfosuccinate, Phenoxyethanol, Blue 1 (CI 42090), Methylparaben, Propylparaben, Ethylparaben, Glycerin, Diamond powder, Pearl Powder, Polysorbate 80, Platinum Powder

PURPOSE

Purpose: Eye Liner

CAUTION

CAUTION: 1. Discontinue use and consult a doctor when - your skin irritates, swells, itches, shows spots on areas applied - your skin reacts similarly with above when exposed to sunlight 2. Avoid applying on wounded, irritated, troubled areas 3. After the use - keep the cap closed - keep it out of children's reach - keep it away from expose to sunlight, high and low temperatures

KEEP OUT OF REACH OF CHILDREN

keep it out of children's reach

INSTRUCTIONS

INSTRUCTIONS: Liquid eyeliner that allows endless vivid drawing. Soft, smudge-proof and easily-washable type eyeliner creates perfectly defined eyes without irritating skin around the eyes

Directions

Directions: Line along the upper lash line following the contour of the eye. Flare outward for more drama or create your own unique design.